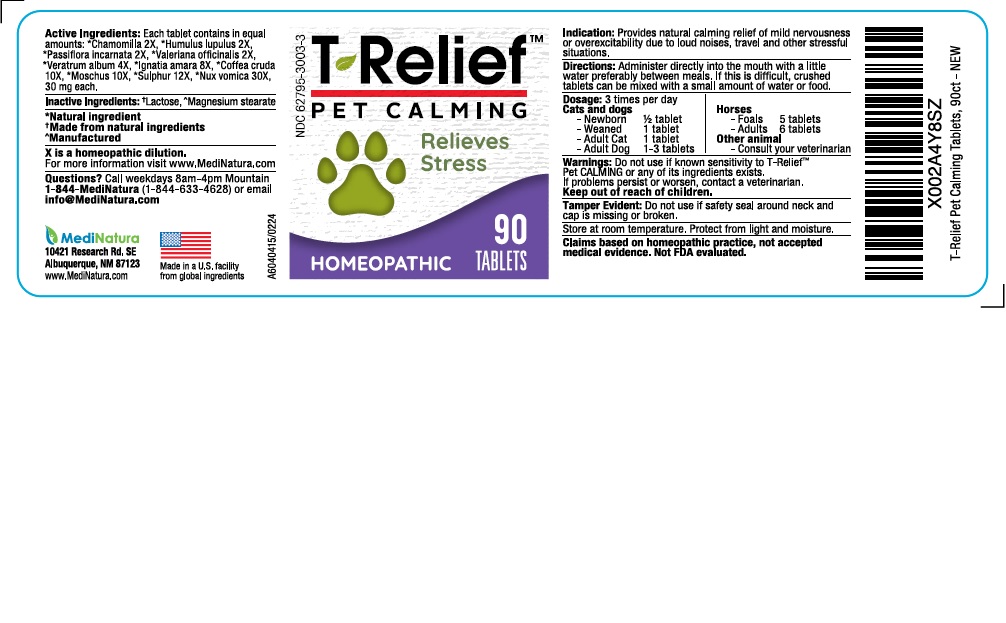 DRUG LABEL: T-Relief Pet Calming
NDC: 62795-3003 | Form: TABLET
Manufacturer: MediNatura New Mexico Inc
Category: homeopathic | Type: OTC ANIMAL DRUG LABEL
Date: 20241211

ACTIVE INGREDIENTS: MATRICARIA CHAMOMILLA 2 [hp_X]/1 1; HOPS 2 [hp_X]/1 1; PASSIFLORA INCARNATA FLOWERING TOP 2 [hp_X]/1 1; VALERIAN 2 [hp_X]/1 1; VERATRUM ALBUM ROOT 4 [hp_X]/1 1; STRYCHNOS IGNATII SEED 8 [hp_X]/1 1; ARABICA COFFEE BEAN 10 [hp_X]/1 1; MOSCHUS MOSCHIFERUS MUSK SAC RESIN 10 [hp_X]/1 1; SULFUR 12 [hp_X]/1 1; STRYCHNOS NUX-VOMICA SEED 30 [hp_X]/1 1
INACTIVE INGREDIENTS: LACTOSE; MAGNESIUM STEARATE

T-Relief Pet Calming

WARNINGS

Do not use if known sensitivity to T-Relief Pet Calming or any of its ingredients exists.
If problems persist or worsen, contact a veterinarian.

INACTIVE INGREDIENTS

Lactose, Magnesium Stearate

USES

Provides natural calming relief of mild nervousness or over excitability due to loud noises, travel and other stressful situations.

Indications

Provides natural calming relief of mild nervousness or over excitability due to loud noises, travel and other stressful situations.

DIRECTIONS

Administer directly into the mouth with a little water preferably between meals. If this is difficult, crushed tablets can be mixed with small amount of water or food.

KEEP OUT OF REACH OF CHILDREN SECTION

PACKAGE LABEL

Add image transcription here...